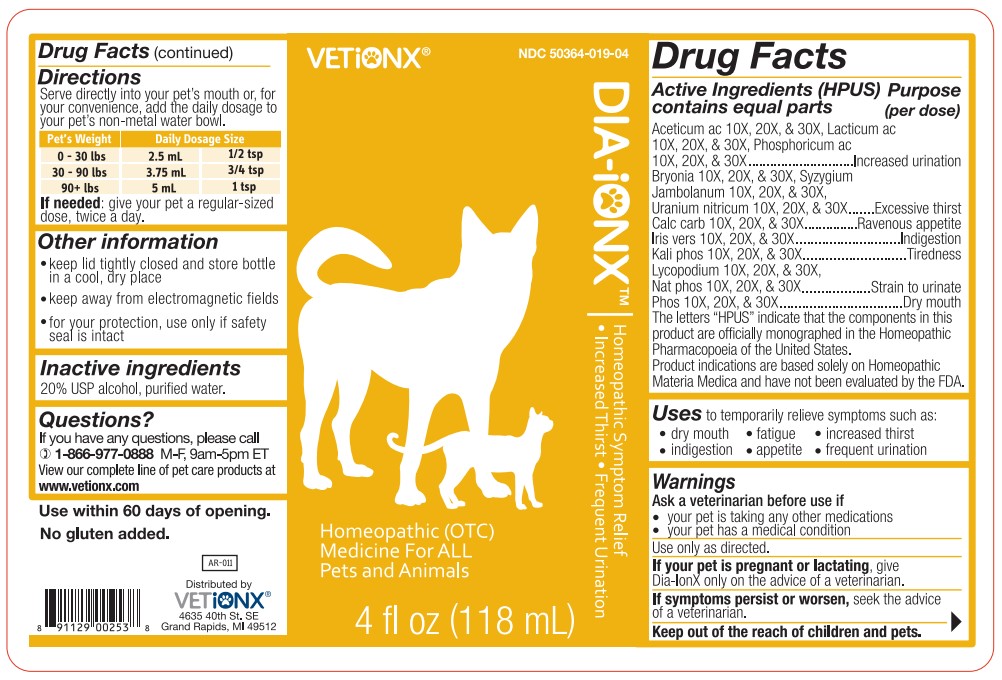 DRUG LABEL: Dia-Ionx
NDC: 50364-019 | Form: LIQUID
Manufacturer: Ionx Health d/b/a VetIonx
Category: homeopathic | Type: OTC ANIMAL DRUG LABEL
Date: 20180410

ACTIVE INGREDIENTS: ACETIC ACID 10 [hp_X]/118 mL; LACTIC ACID, DL- 10 [hp_X]/118 mL; PHOSPHORIC ACID 10 [hp_X]/118 mL; BRYONIA ALBA ROOT 10 [hp_X]/118 mL; SYZYGIUM CUMINI SEED 10 [hp_X]/118 mL; URANYL NITRATE HEXAHYDRATE 10 [hp_X]/118 mL; OYSTER SHELL CALCIUM CARBONATE, CRUDE 10 [hp_X]/118 mL; IRIS VERSICOLOR ROOT 10 [hp_X]/118 mL; DIBASIC POTASSIUM PHOSPHATE 10 [hp_X]/118 mL; LYCOPODIUM CLAVATUM SPORE 10 [hp_X]/118 mL; SODIUM PHOSPHATE, DIBASIC, HEPTAHYDRATE 10 [hp_X]/118 mL; PHOSPHORUS 10 [hp_X]/118 mL
INACTIVE INGREDIENTS: ALCOHOL; WATER

ACTIVE INGREDIENT

Aceticum ac 10X, 20X, & 30X, Lacticum ac 10X, 20X, & 30X, Phosphoricum ac 10X, 20X, & 30X
Bryonia 10X, 20X, & 30X, Syzygium Jambolanum 10X, 20X, & 30X, Uranium nitricum 10X, 20X, & 30X
Calc carb 10X, 20X, & 30X
Iris vers 10X, 20X, & 30X
Kali phos 10X, 20X, & 30X
Lycopodium 10X, 20X, & 30X Nat phos 10X, 20X, & 30X
Phos 10X, 20X, & 30X

PURPOSE

Aceticum ac 10X, 20X, & 30X, Lacticum ac 10X, 20X, & 30X, Phosphoricum ac 10X, 20X, & 30X ....... Increased urination
Bryonia 10X, 20X, & 30X, Syzygium Jambolanum 10X, 20X, & 30X, Uranium nitricum 10X, 20X, & 30X ........ Excessive thirst
Calc carb 10X, 20X, & 30X ....... Ravenous appetite
Iris vers 10X, 20X, & 30X ....... Indigestion
Kali phos 10X, 20X, & 30X ....... Tiredness
Lycopodium 10X, 20X, & 30X Nat phos 10X, 20X, & 30X ....... Strain to urinate
Phos 10X, 20X, & 30X ....... Dry mouth

The letters “HPUS” indicate that the components in this product are officially monographed in the Homeopathic Pharmacopoeia of the United States.
Product indications are based solely on Homeopathic Materia Medica and have not been evaluated by the FDA.

INDICATIONS AND USAGE

To temporarily relieve symptoms such as:

- dry mouth
- fatigue
- increased thirst
- indigestion
- appetite
- frequent urination

WARNINGS

Ask a veterinarian before use if

- your pet is taking any other medication
- your pet has a medical condition

WARNINGS

Use only as directed.

PREGNANCY OR BREAST FEEDING

If your pet is pregnant or lactating, give Dia-Ionx only on the advice of a veterinarian.

WHEN USING

If symptoms persist or worsen, seek the advice of a veterinarian.

KEEP OUT OF REACH OF CHILDREN

Keep out of the reach of chidlren and pets.

DOSAGE AND ADMINISTRATION

Serve directly into your pet's mouth or, for your convenience, add the daily dosage to your pet's non-metal water bowl.

Pet's Weight | Daily Dosage Size
0 - 30 lbs | 2.5 mL | 1/2 tsp
30 - 90 lbs | 3.75 mL | 3/4 tsp
90+ lbs | 5 mL | 1 tsp

STORAGE AND HANDLING

- keep lid tightly closed and store bottle in a cool, dry place
- keep away from electromagnetic fields
- for your protection, use only if safety seal is intact

INACTIVE INGREDIENT

20% USP alcohol, purified water.

QUESTIONS

If you have any questions, please call 1-866-977-0888 M-F, 9am-5pm ET

View our complete line of pet care products at www.vetionx.com

DESCRIPTION

Use within 60 days of opening.

No gluten added.

Distributed by

VetIonx

4635 40th St. SE

Grand Rapids, MI 49512

PACKAGE LABEL

NDC 50364-019-04

VETIONX

DIA-IONXTM

Homeopathic Symptom Relief

- Increased Thirst
- Frequent Urination

Homeopathic (OTC) Medicine for ALL Pets and Animals

4 fl oz (118 mL)